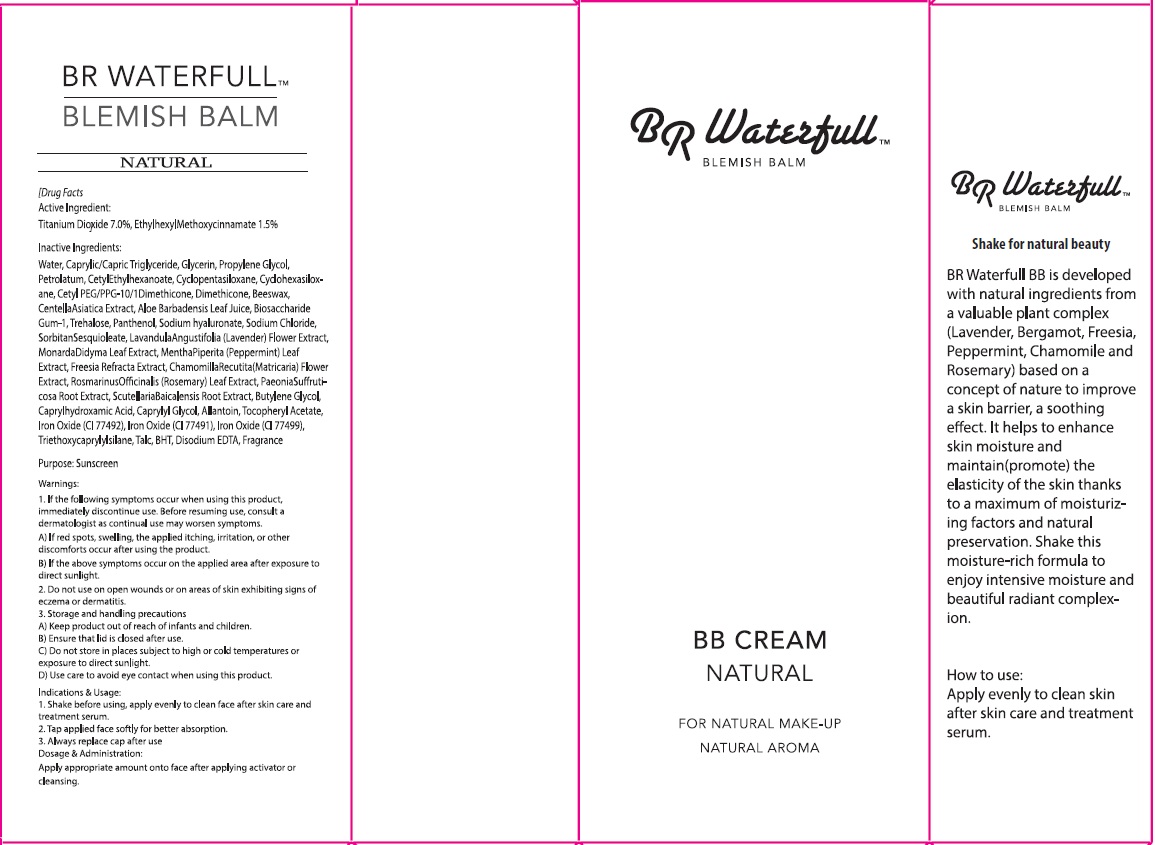 DRUG LABEL: BR Waterfull BB BLEMISH BALM NATURAL
NDC: 70619-020 | Form: CREAM
Manufacturer: BR
Category: otc | Type: HUMAN OTC DRUG LABEL
Date: 20160418

ACTIVE INGREDIENTS: Titanium Dioxide 2.8 g/40 g; Octinoxate 0.6 g/40 g
INACTIVE INGREDIENTS: Water; Glycerin

ACTIVE INGREDIENT

Active Ingredient: Titanium Dioxide 7.0%, Ethylhexyl Methoxycinnamate 1.5%

INACTIVE INGREDIENT

Inactive Ingredients: Water, Caprylic/Capric Triglyceride, Glycerin, Propylene Glycol, Petrolatum, Cetyl Ethylhexanoate, Cyclopentasiloxane, Cyclohexasiloxane, Cetyl PEG/PPG-10/1Dimethicone, Dimethicone, Beeswax, Centella Asiatica Extract, Aloe Barbadensis Leaf Juice, Biosaccharide Gum-1, Trehalose, Panthenol, Sodium hyaluronate, Sodium Chloride, Sorbitan Sesquioleate, Lavandula Angustifolia (Lavender) Flower Extract, Monarda Didyma Leaf Extract, Mentha Piperita (Peppermint) Leaf Extract, Freesia Refracta Extract, Chamomilla Recutita(Matricaria) Flower Extract, Rosmarinus Officinalis (Rosemary) Leaf Extract, Paeonia Suffruticosa Root Extract, Scutellaria Baicalensis Root Extract, Butylene Glycol, Caprylhydroxamic Acid, Caprylyl Glycol, Allantoin, Tocopheryl Acetate, Iron Oxide (CI 77492), Iron Oxide (CI 77491), Iron Oxide (CI 77499), Triethoxycaprylylsilane, Talc, BHT, Disodium EDTA, Fragrance

PURPOSE

Purpose: Sunscreen

WARNINGS

Warnings: 1. If the following side effects occur, immediately discontinue use. Before resuming use, consult a dermatologist as continual use may worsen symptoms. A) If red spots, swelling, itching, irritation, or other discomforts occur after using the product. B) If the above symptoms occur on the applied area after exposure to direct sunlight. 2. Do not use on open wounds or on areas of skin exhibiting signs of eczema or dermatitis. 3. Storage and handling precautions A) Keep product out of reach of infants and children. B) Ensure that lid is closed after use. C) Do not store in places subject to high or cold temperatures or under exposure to direct sunlight. D) Use care to avoid eye contact when using this product.

DESCRIPTION

Indications & Usage: 1. Shake before using, apply evenly to clean face after skin care and treatment serum. 2. Tap applied face softly for better absorption. 3. Always replace cap after use

Dosage & Administration: Apply appropriate amount onto face after applying activator or cleansing.